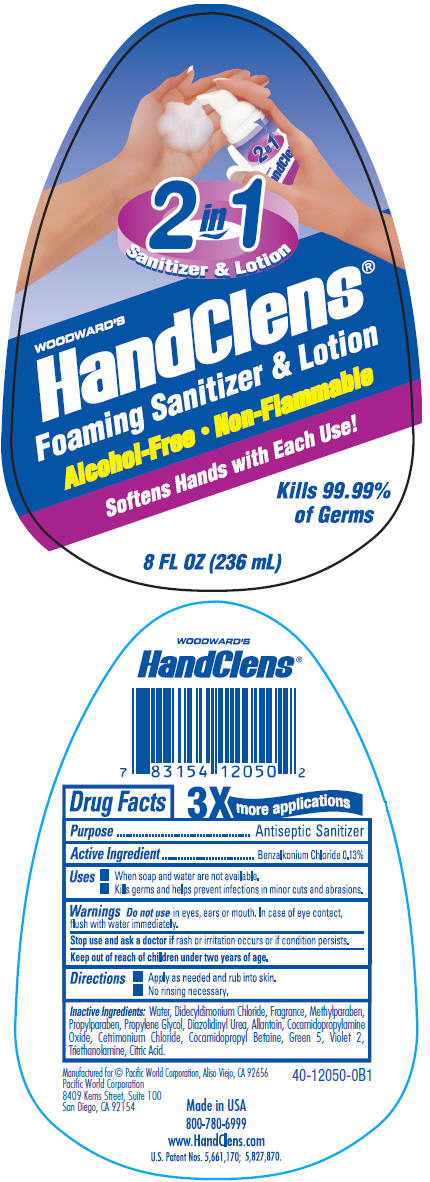 DRUG LABEL: Woodwards HandClens Foaming Sanitizer
NDC: 60193-200 | Form: LIQUID
Manufacturer: Pacific World Corporation
Category: otc | Type: HUMAN OTC DRUG LABEL
Date: 20141020

ACTIVE INGREDIENTS: BENZALKONIUM CHLORIDE 1.3 mg/1 mL
INACTIVE INGREDIENTS: WATER; DIDECYLDIMONIUM CHLORIDE; METHYLPARABEN; PROPYLPARABEN; PROPYLENE GLYCOL; DIAZOLIDINYL UREA; ALLANTOIN; COCAMIDOPROPYLAMINE OXIDE; CETRIMONIUM CHLORIDE; COCAMIDOPROPYL BETAINE; D&C GREEN NO. 5; EXT. D&C VIOLET NO. 2; TROLAMINE; ALCOHOL

Woodward's HandClens® Foaming Sanitizer & Lotion

Drug Facts

Active Ingredients

Benzalkonium Chloride 0.13%

Purpose

Antiseptic Sanitizer

Uses

When soap and water are not available.

Kills germs and helps prevent infections in minor cuts and abrasions.

WARNINGS

Do not use in eyes,ears or mouth. In case of eye contact, flush with water immediately.

Stop use and ask a doctor if rash or irritation occurs or if condition persists.

Keep out of reach of children under 2 years of age.

Directions

Apply as needed and rub into skin. No rinsing necessary.

Inactive Ingredients

Water, Didecyldimonium Chloride, Fragrance, Methylparaben, Propylparaben, Propylene Glycol, Diazolidinyl Urea, Allantoin, Cocamidopropylamine Oxide, Cetrimonium Chloride, Cocamidopropyl Betaine, Green 5, Violet 2, Triethanolamine, Citric Acid

PRINCIPAL DISPLAY PANEL - 236 mL Bottle Label

2 in 1
Sanitizer & Lotion

WOODWARD'S
HandClens®

Foaming Sanitizer & Lotion

Alcohol-Free • Non-Flammable

Softens Hands with Each Use!

Kills 99.99%
of Germs

8 FL OZ (236 mL)